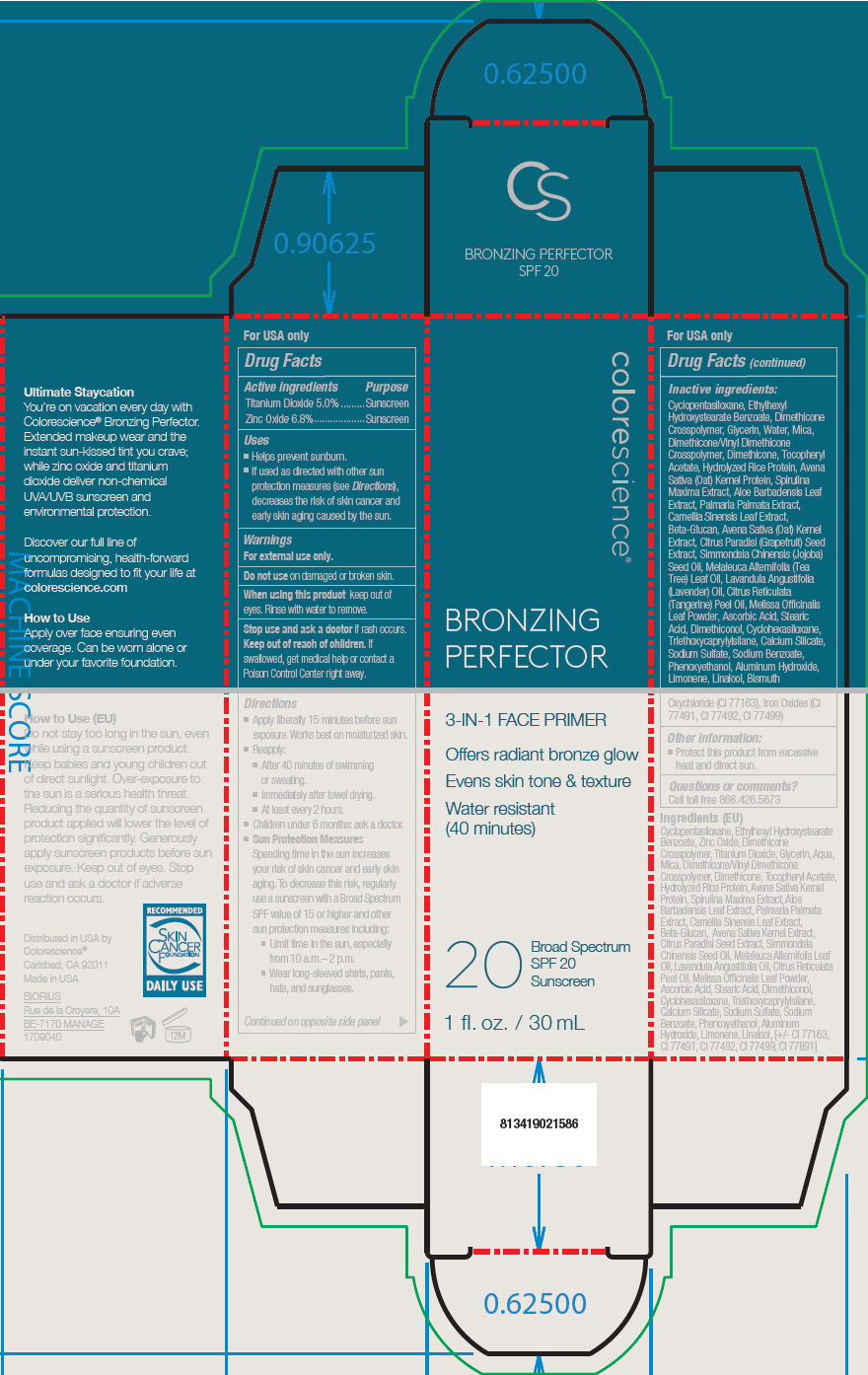 DRUG LABEL: Bronzing Perfector SPF 20 Sunscreen
NDC: 68078-016 | Form: LIQUID
Manufacturer: Colorescience
Category: otc | Type: HUMAN OTC DRUG LABEL
Date: 20181105

ACTIVE INGREDIENTS: Titanium Dioxide 50 mg/1 mL; Zinc Oxide 68 mg/1 mL
INACTIVE INGREDIENTS: Cyclomethicone 5; Ethylhexyl Hydroxystearate Benzoate; Dimethicone Crosspolymer (450000 MPA.S AT 12% IN CYCLOPENTASILOXANE); Glycerin; Water; Mica; Dimethicone/Vinyl Dimethicone Crosspolymer (Soft Particle); Dimethicone; .Alpha.-Tocopherol Acetate; Rice Bran; Oat; ARTHROSPIRA MAXIMA; Aloe Vera Leaf; Dulse; Green Tea Leaf; Polysaccharide-K; Citrus Paradisi Seed; Jojoba Oil; Tea Tree Oil; Lavender Oil; CITRUS RETICULATA LEAF OIL; Melissa Officinalis Leaf; Ascorbic Acid; Stearic Acid; Dimethiconol (100000 CST); Cyclomethicone 6; Triethoxycaprylylsilane; Calcium Silicate; Sodium Sulfate; Sodium Benzoate; Phenoxyethanol; Aluminum Hydroxide; Limonene, (+)-; Bismuth Oxychloride; FERRIC OXIDE YELLOW; FERRIC OXIDE RED; FERROSOFERRIC OXIDE; LINALOOL, (+/-)-

Bronzing Perfector SPF 20 Sunscreen

Drug Facts

ACTIVE INGREDIENT

Active ingredients | Purpose
Titanium Dioxide 5.0% | Sunscreen
Zinc Oxide 6.8% | Sunscreen

Uses

- Helps prevent sunburn.
- If used as directed with other sun protection measures (see Directions), decreases the risk of skin cancer and early skin aging caused by the sun.

Warnings

For external use only.

Do not use on damaged or broken skin.

When using this product keep out of eyes. Rinse with water to remove.

Stop use and ask a doctor if rash occurs.

Keep out of reach of children. If swallowed, get medical help or contact a Poison Control Center right away.

Directions

- Apply liberally 15 minutes before sun exposure. Works best on moisturized skin.
- Reapply:
  - After 40 minutes of swimming or sweating.
  - Immediately after towel drying.
  - At least every 2 hours.
- Children under 6 months: ask a doctor
- Sun Protection Measures
  Spending time in the sun increases your risk of skin cancer and early skin aging. To decrease this risk, regularly use a sunscreen with a Broad Spectrum SPF value of 15 or higher and other sun protection measures including:
  - Limit time in the sun, especially from 10 a.m.– 2 p.m.
  - Wear long-sleeved shirts, pants, hats, and sunglasses.

Inactive ingredients

Cyclopentasiloxane, Ethylhexyl Hydroxystearate Benzoate, Dimethicone Crosspolymer, Glycerin, Water, Mica, Dimethicone/Vinyl Dimethicone Crosspolymer, Dimethicone, Tocopheryl Acetate, Hydrolyzed Rice Protein, Avena Sativa (Oat) Kernel Protein, Spirulina Maxima Extract, Aloe Barbadensis Leaf Extract, Palmaria Palmata Extract, Camellia Sinensis Leaf Extract, Beta-Glucan, Avena Sativa (Oat) Kernel Extract, Citrus Paradisi (Grapefruit) Seed Extract, Simmondsia Chinensis (Jojoba) Seed Oil, Melaleuca Alternifolia (Tea Tree) Leaf Oil, Lavandula Angustifolia (Lavender) Oil, Citrus Reticulata (Tangerine) Peel Oil, Melissa Officinalis Leaf Powder, Ascorbic Acid, Stearic Acid, Dimethiconol, Cyclohexasiloxane, Triethoxycaprylylsilane, Calcium Silicate, Sodium Sulfate, Sodium Benzoate, Phenoxyethanol, Aluminum Hydroxide, Limonene, Linalool, Bismuth Oxychloride (CI 77163), Iron Oxides (CI 77491, CI 77492, CI 77499)

Other information

- Protect this product from excessive heat and direct sun.

Questions or comments?

Call toll free 866.426.5673

Distributed in USA by
Colorescience®
Carlsbad, CA 92011

PRINCIPAL DISPLAY PANEL - 30 mL Tube Carton

colorescience®

BRONZING
PERFECTOR

3-IN-1 FACE PRIMER

Offers radiant bronze glow

Evens skin tone & texture

Water resistant
(40 minutes)

20
Broad Spectrum
SPF 20
Sunscreen

1 fl. oz. / 30 mL